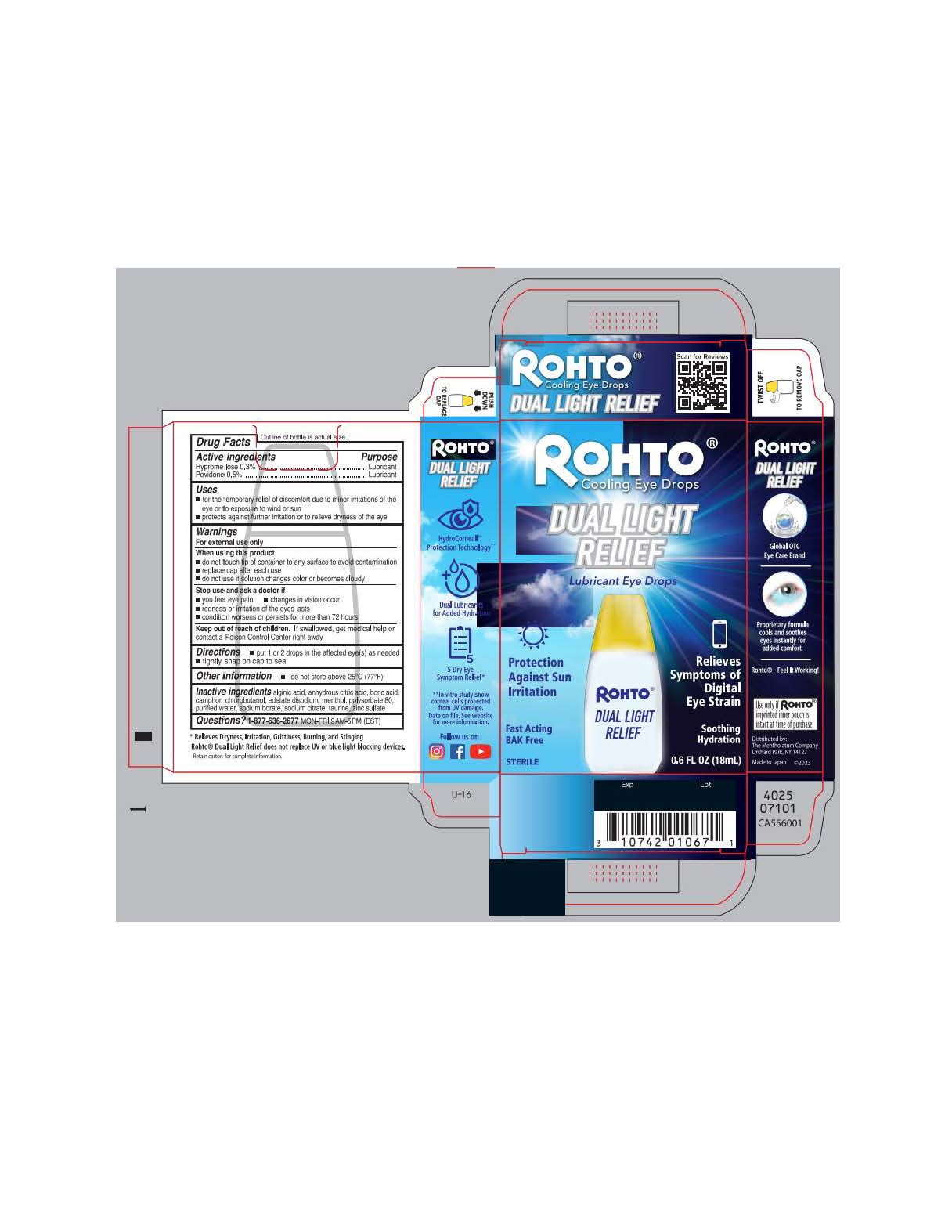 DRUG LABEL: Rohto
NDC: 10742-8459 | Form: LIQUID
Manufacturer: The Mentholatum Company
Category: otc | Type: HUMAN OTC DRUG LABEL
Date: 20241219

ACTIVE INGREDIENTS: POVIDONE 5 mg/1 mL; HYPROMELLOSE, UNSPECIFIED 3 mg/1 mL
INACTIVE INGREDIENTS: LEVOMENTHOL; EDETATE DISODIUM; BORIC ACID; CHLOROBUTANOL; TRISODIUM CITRATE DIHYDRATE; ZINC SULFATE HEPTAHYDRATE; ALGINIC ACID; ANHYDROUS CITRIC ACID; POLYSORBATE 80; SODIUM BORATE; TAURINE; WATER; CAMPHOR (SYNTHETIC)

Drug Facts - Rohto Dual Light Relief

Active ingredient

Hypromellose 0.3%

Povidone 0.5%

Purpose

Hypromellose – Lubricant

Povidone - Lubricant

Uses

- for the temporary relief of discomfort due to minor irritations of the eye or to exposure to wind or sun
- protects against further irritation or to relieve dryness of the eye

Warnings

For external use only

When using this product

- do not touch tip of container to any surface to avoid contamination
- replace cap after each use
- do not use if solution changes color or becomes cloudy

Stop use and ask a doctor if

- you feel eye pain
- changes in vision occur
- redness or irritation of the eyes lasts
- condition worsens or persists for more than 72 hours

Keep out of reach of children.

If swallowed, get medical help or contact a Poison Control Center right away.

Directions

- put 1 or 2 drops in the affected eye(s) as needed
- tightly snap on cap to seal

Other information

- do not store above 25OC (77OF)

Inactive ingredients

alginic acid, anhydrous citric acid, boric acid, camphor, chlorobutanol, edetate disodium, menthol, polysorbate 80, purified water, sodium borate, sodium citrate, taurine, zinc sulfate

Questions?

1-877-636-2677 MON-FRI 9AM-5PM (EST)